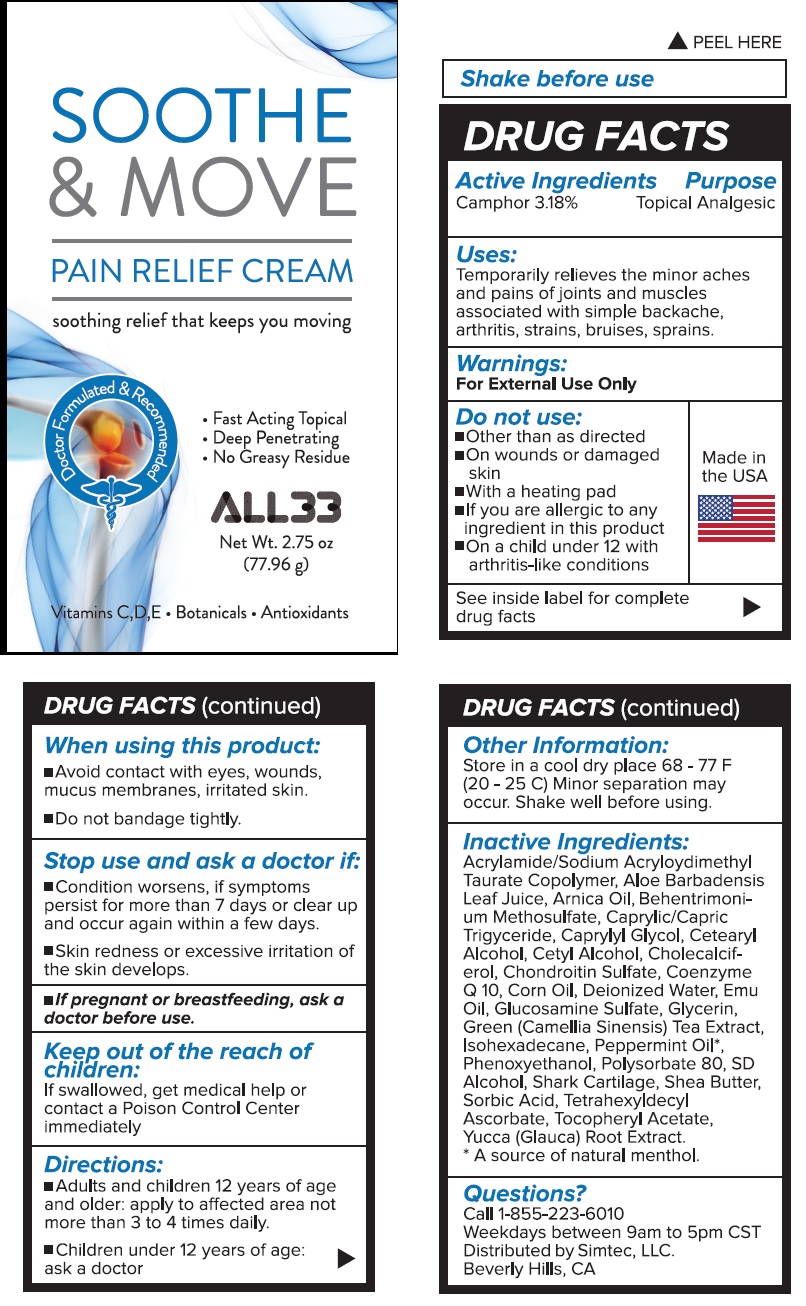 DRUG LABEL: Soothe and Move Pain Relief Cream
NDC: 78805-005 | Form: CREAM
Manufacturer: Simtec LLC
Category: otc | Type: HUMAN OTC DRUG LABEL
Date: 20211123

ACTIVE INGREDIENTS: CAMPHOR (SYNTHETIC) 3.18 g/100 g
INACTIVE INGREDIENTS: SODIUM ACRYLOYLDIMETHYLTAURATE-ACRYLAMIDE COPOLYMER (1:1; 90000-150000 MPA.S); ALOE VERA LEAF; ARNICA MONTANA FLOWER; BEHENTRIMONIUM METHOSULFATE; MEDIUM-CHAIN TRIGLYCERIDES; CAPRYLYL GLYCOL; CETOSTEARYL ALCOHOL; CETYL ALCOHOL; CHOLECALCIFEROL; CHONDROITIN SULFATE (BOVINE); UBIDECARENONE; CORN OIL; WATER; EMU OIL; GLUCOSAMINE SULFATE; GLYCERIN; GREEN TEA LEAF; ISOHEXADECANE; PEPPERMINT OIL; PHENOXYETHANOL; POLYSORBATE 80; ALCOHOL; SHARK CARTILAGE; SHEA BUTTER; SORBIC ACID; TETRAHEXYLDECYL ASCORBATE; .ALPHA.-TOCOPHEROL ACETATE; YUCCA GLAUCA ROOT

SOOTHE & MOVE PAIN RELIEF CREAM

DRUG FACTS

Active Ingredients
Camphor 3.18%

Purpose
Topical Analgesic

Uses:
Temporarily relieves the minor aches
and pains of joints and muscles
associated with simple backache,
arthritis, strains, bruises, sprains.

Warnings:
For External Use Only

Do not use:
■ Other than as directed
■ 0n wounds or damaged
skin
■ With a heating pad
■ If you are allergic to any
ingredient in this product
■ 0n a child under 12 with
arthritis-like conditions

When using this product:
■ Avoid contact with eyes, wounds,
mucus membrane, irritated skin.
■ Do not bandage tightly.

Stop use and ask a doctor if:
■Condition worsens, if symptoms
persist for more than 7 days or clear up
and occur again within a few days.
■Skin redness or excessive irritation of
the skin develops.

PREGNANCY OR BREAST FEEDING

■ If pregnant or breastfeedlng, ask a
doctor before use.

Keep out ofthe reach of
chilaren:
If swallowed, get medical help or
contact a Poison Control Center
immediately

Directions:
■ Adults and children 12 years of age
and older: apply to affected area not
more than 3 to 4 times dally.
■ Children under 12 years of age:
ask a doctor

Other Information:
Store in a cool dry place 68 - 77 F
(20 - 25 C) Minor separation may
occur. Shake well before using.

Inactive Ingredients:
Acrylamide/Sodium Acryloyldimethyl
Taurate Copolymer, Aloe Barbadensis
Leaf Juice, Arnica Oil, Behentrimonium
Methosulfate, Caprylic/Capric
Triglyceride, Capryly1 Glycol, Cetearyl
Alcohol, Cetyl Alcohol, Cholecalciferol,
Chondroitin Sulfate, Coenzyme
Q 10, Corn Oil, Deionized Water, Emu
Oil, Glucosamine Sulfate, Glycerin,
Green (Camellia Sinensis) Tea Extract,
Isohexadecane, Peppermint Oil*,
Phenoxyethanol, Polysorbate 80, SO
Alcohol, Shark cartilage, Shea Butter,
Sorbic Acid, Tetrahexyldecyl
Ascorbate, Tocopheryl Acetate,
Yucca (Glauca) Root Extract.
*A source of natural menthol.

QUESTIONS

Ouestlons?
Call 1-855-223-6010
Weekdays between 9am to 5pm CST

PACKAGE LABELING - PRINCIPAL DISPLAY PANEL

SOOTHE & MOVE
PAIN RELIEF CREAM

soothing relief that keeps you moving

Doctor Formulated & Recommended

• Fast Acting Topical
• Deep Penetrating
• No Greasy Residue

ALL33
Net Wt. 2.75 Oz
(77.96 g)
Vitamin C, D, E • Botanicals • Antioxidants

Shake before use

Ouestlons?
call 1-855-223-6010
Weekdays betwean 9am to 5pm CST
Distributed by Simtec, LLC.
Beverly Hills, CA

RES